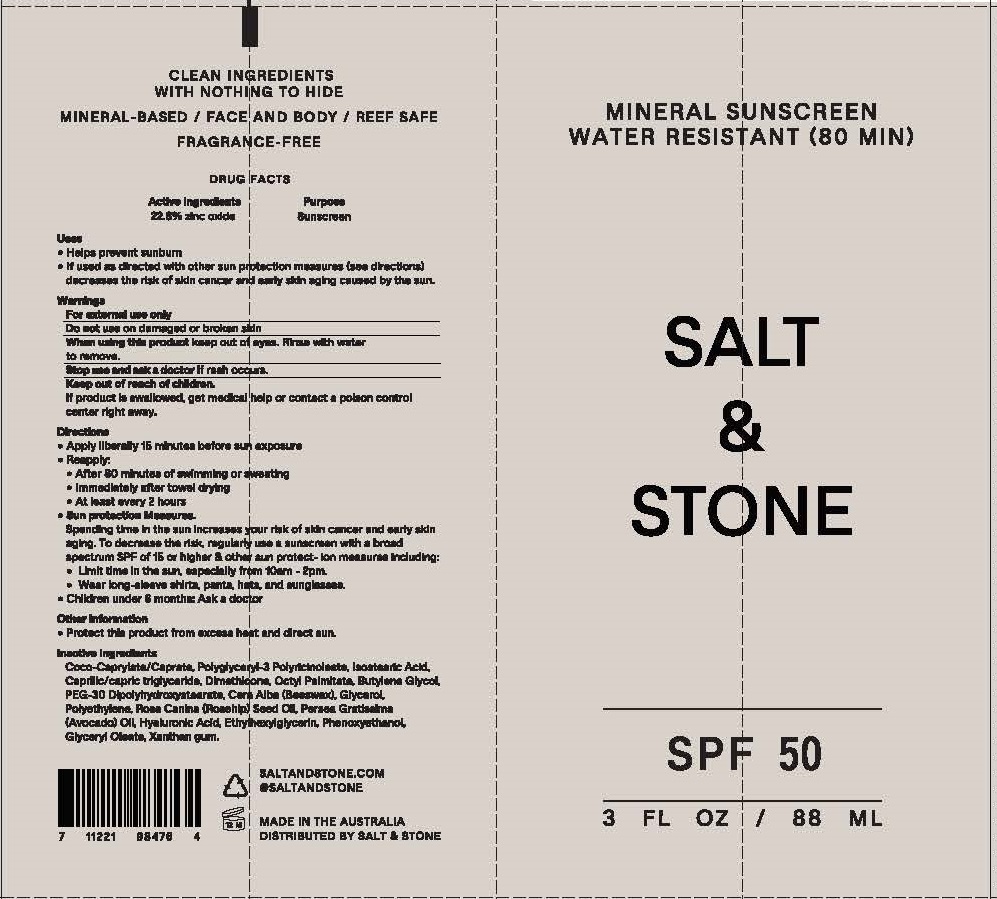 DRUG LABEL: MINERAL SUNSCREEN - WATER RESISTANT
NDC: 71585-109 | Form: LOTION
Manufacturer: SALT AND STONE
Category: otc | Type: HUMAN OTC DRUG LABEL
Date: 20190728

ACTIVE INGREDIENTS: ZINC OXIDE 22.8 g/100 mL
INACTIVE INGREDIENTS: COCO-CAPRYLATE/CAPRATE; POLYGLYCERYL-3 RICINOLEATE; ISOSTEARIC ACID; MEDIUM-CHAIN TRIGLYCERIDES; DIMETHICONE; ETHYLHEXYL PALMITATE; BUTYLENE GLYCOL; PEG-30 DIPOLYHYDROXYSTEARATE; YELLOW WAX; GLYCERIN; HIGH DENSITY POLYETHYLENE; ROSA CANINA SEED; AVOCADO OIL; HYALURONIC ACID; ETHYLHEXYLGLYCERIN; PHENOXYETHANOL; GLYCERYL MONOOLEATE; XANTHAN GUM

SALT & STONE MINERAL SUNSCREEN SPF-50 - WATER RESISTANT

ACTIVE INGREDIENTS

ZINC OXIDE 22.8%

PURPOSE

SUNSCREEN

USE

- HELPS PREVENT SUNBURN.
- If used as directed with other sun protection measures (see directions) decreases the risk of skin cancer and early skin
  aging caused by the sun.

WARNINGS

For external use only
Do not use on damaged or broken skin
When using this product keep out of eyes. Rinse with water to remove.
Stop use and ask a doctor if rash occurs.

KEEP OUT OF REACH OF CHILDREN.

IF PRODUCT IS SWALLOWED, GET MEDICAL HELP OR CONTACT A POISON CONTROL CENTER RIGHT AWAY.

DIRECTIONS

• Apply liberally 15 minutes before sun exposure
• Reapply:
• After 80 minutes of swimming or sweating
• Immediately after towel drying
• At least every 2 hours
• Sun Protection Measures.
Spending time in the sun increases your risk of skin cancer and early skin aging. To decrease the risk, regularly use a sunscreen with a broad spectrum SPF of 15 or higher & other sun protection measures including:
• Limit time in the sun, especially from 10am - 2pm.
• Wear long-sleeve shirts, pants, hats, and sunglasses.
• Children under 6 months: Ask a doctor

INACTIVE INGREDIENTS

Coco-Caprylate/Caprate, Polyglyceryl-3 Polyricinoleate, Isostearic Acid, Caprilic/capric triglyceride, Dimethicone, Octyl Palmitate, Butylene Glycol, PEG-30 Dipolyhydroxystearate, Cera Alba (Beeswax), Glycerol, Polyethylene, Rosa Canina (Rosehip) Seed Oil, Persea Gratissima (Avocado) Oil, Hyaluronic Acid, Ethylhexylglycerin, Phenoxyethanol, Glyceryl Oleate, Xanthan gum.

OTHER INFORMATION

- PROTECT THIS PRODUCT FROM EXCESSIVE HEAT AND DIRECT SUN